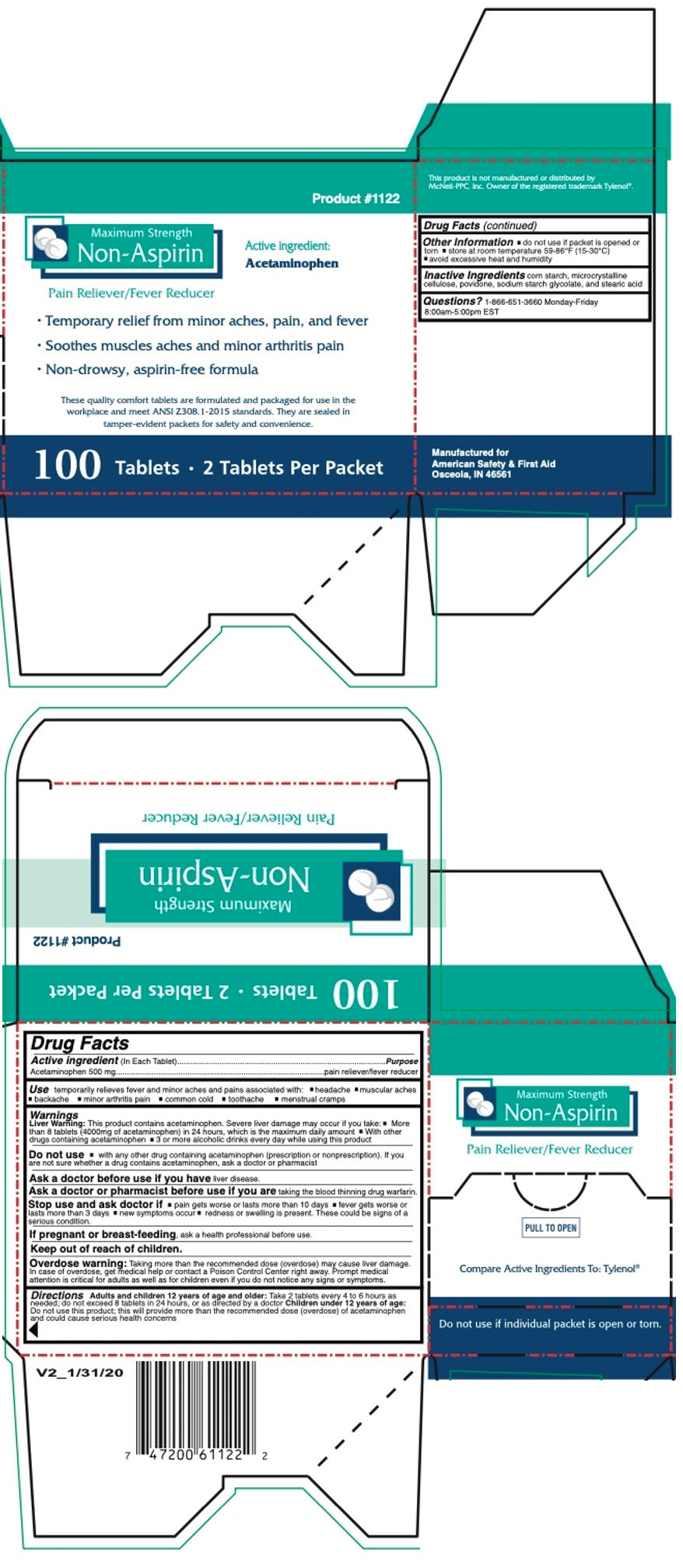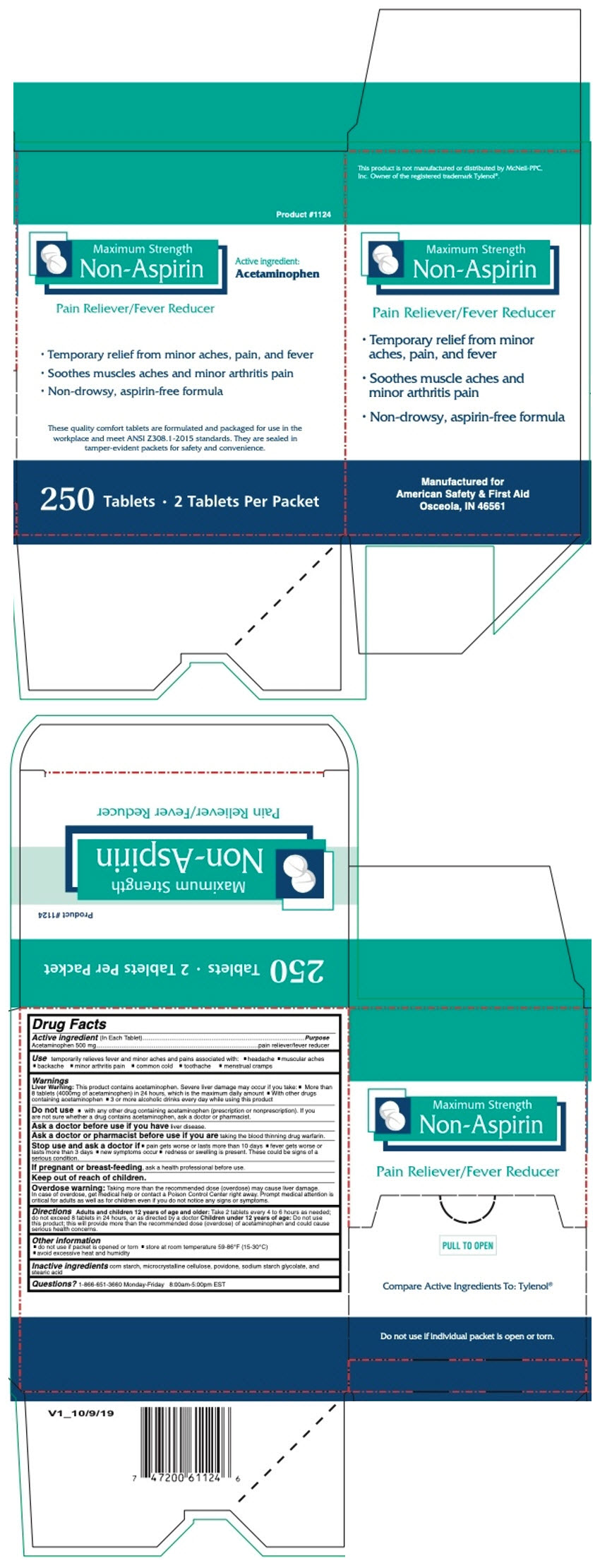 DRUG LABEL: MAXIMUM STRENGTH NON-ASPIRIN 100
NDC: 73598-1122 | Form: TABLET
Manufacturer: JHK Inc dba American Safety & First Aid
Category: otc | Type: HUMAN OTC DRUG LABEL
Date: 20251216

ACTIVE INGREDIENTS: ACETAMINOPHEN 500 mg/1 1
INACTIVE INGREDIENTS: STARCH, CORN; MICROCRYSTALLINE CELLULOSE; POVIDONE, UNSPECIFIED; SODIUM STARCH GLYCOLATE TYPE A; STEARIC ACID

MAXIMUM STRENGTH NON-ASPIRIN

Drug Facts

Active ingredient (In Each Tablets)

Acetaminophen 500 mg

Purpose

pain reliever/fever reducer

Use

temporarily relieves fever and minor aches and pains associated with:

- headache
- backache
- muscular aches
- minor arthritis pain
- common cold
- toothaches
- menstrual cramps

Warnings

Liver Warning

This product contains acetaminophen. Severe liver damage may occur if you take:

- More than 8 tablets (4000mg of acetaminophen) in 24 hours, which is the maximum daily amount
- With other drugs containing acetaminophen
- 3 or more alcoholic drinks every day while using this product

Do not use

- with any other drug containing acetaminophen (prescription or nonprescription). If you are not sure whether a drug contains acetaminophen, ask a doctor or pharmacist

Ask a doctor before use if you have liver disease.

Ask a doctor or pharmacist before use if you are taking the blood thinning drug warfarin.

Stop use and ask doctor if

- pain gets worse or lasts more than 10 days
- fever gets worse or lasts more than 3 days
- new symptoms occur
- redness or swelling is present. These could be signs of a serious condition.

PREGNANCY OR BREAST FEEDING

If pregnant or breast-feeding, ask a health professional before use.

Keep out of reach of children.

Overdose warning

Taking more than the recommended dose (overdose) may cause liver damage. In case of overdose, get medical help or contact a Poison Control Center right away. Prompt medical attention is critical for adults as well as for children even if you do not notice any signs or symptoms.

Directions

Adults and children 12 years of age and older: Take 2 tablets every 4 to 6 hours as needed; do not exceed 8 tablets in 24 hours, or as directed by a doctor Children under 12 years of age: Do not use this product; this will provide more than the recommended dose (overdose) of acetaminophen and could cause serious health concerns

Other Information

- do not use if packet is opened or torn
- store at room temperature 59-86℉ (15-30℃)
- avoid excessive heat and humidity

Inactive Ingredients

corn starch, microcrystalline cellulose, povidone, sodium starch glycolate, and stearic acid

Questions?

1-866-651-3660 Monday-Friday 8:00am-5:00pm EST

PRINCIPAL DISPLAY PANEL - 100 Tablet Box

Product #1122

Maximum Strength
Non-Aspirin

Active ingredient:
Acetaminophen

Pain Reliever/Fever Reducer

- Temporary relief from minor aches, pain, and fever
- Soothes muscles aches and minor arthritis pain
- Non-drowsy, aspirin-free formula

These quality comfort tablets are formulated and packaged for use in the
workplace and meet ANSI Z308. 1-2015 standards. They are sealed in
tamper-evident packets for safety and convenience.

100 Tablets • 2 Tablets Per Packet

PRINCIPAL DISPLAY PANEL - 250 Tablet Box

Product #1124

Maximum Strength
Non-Aspirin

Active ingredient:
Acetaminophen

Pain Reliever/Fever Reducer

- Temporary relief from minor aches, pain, and fever
- Soothes muscles aches and minor arthritis pain
- Non-drowsy, aspirin-free formula

These quality comfort tablets are formulated and packaged for use in the
workplace and meet ANSI Z308. 1-2015 standards. They are sealed in
tamper-evident packets for safety and convenience.

250 Tablets • 2 Tablets Per Packet